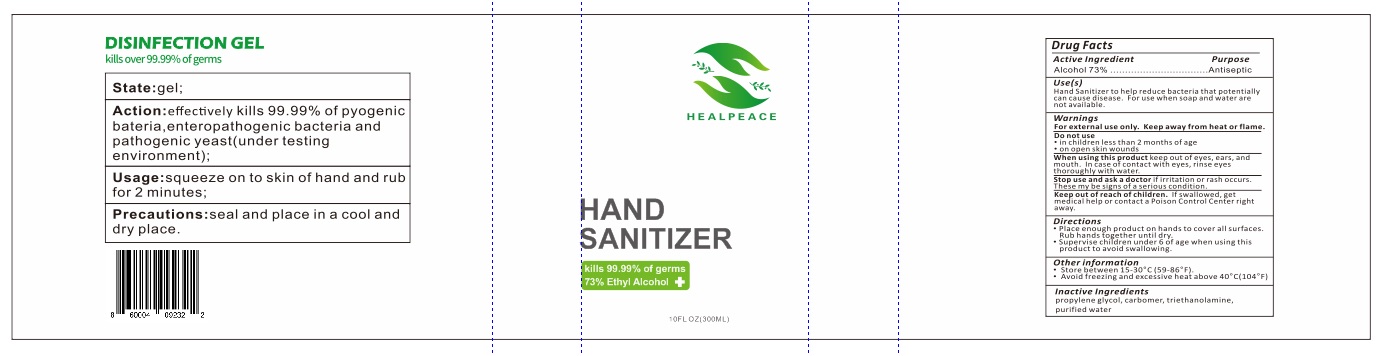 DRUG LABEL: HealPeace
NDC: 75530-123 | Form: GEL
Manufacturer: HealPeace
Category: otc | Type: HUMAN OTC DRUG LABEL
Date: 20201230

ACTIVE INGREDIENTS: ALCOHOL 73 mL/100 mL
INACTIVE INGREDIENTS: TROLAMINE; PROPYLENE GLYCOL; CARBOMER HOMOPOLYMER, UNSPECIFIED TYPE; WATER

INDICATIONS AND USAGE

Hand Sanitizer to help reduce bacteria that potentially can cause disease. For use when soap and water are not available.

ACTIVE INGREDIENT

Alcohol 73% v/v. Purpose: Antiseptic

PURPOSE

Antiseptic, Hand Sanitizer

WARNINGS

For external use only. Flammable. Keep away from heat or flame

DO NOT USE

- in children less than 2 months of age
- on open skin wounds

When using this product keep out of eyes, ears, and mouth. In case of contact with eyes, rinse eyes thoroughly with water.
Stop use and ask a doctor if irritation or rash occurs. These may be signs of a serious condition.
Keep out of reach of children. If swallowed, get medical help or contact a Poison Control Center right away.

Stop use and ask a doctor if irritation or rash occurs. These may be signs of a serious condition.

Keep out of reach of children. If swallowed, get medical help or contact a Poison Control Center right away.

DOSAGE AND ADMINISTRATION

Place enough product on hands to cover all surfaces. Rub hands together until dry.
Supervise children under 6 years of age when using this product to avoid swallowing.

STORAGE AND HANDLING

Store between 15-30C (59-86F)
Avoid freezing and excessive heat above 40C (104F)

INACTIVE INGREDIENT

propylene glycol, carbomer, triethanolamine, purified water

Package Label - Principal Display Panel

300 mL NDC: 75530-123-02